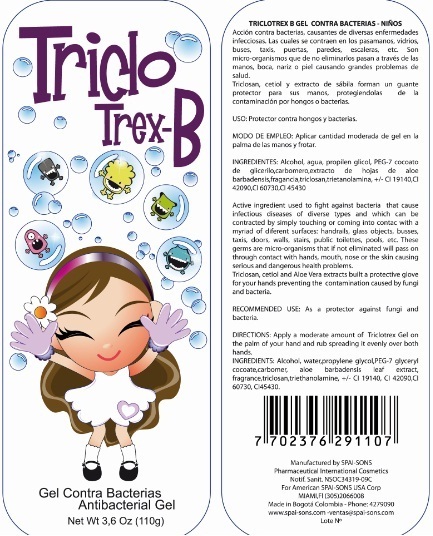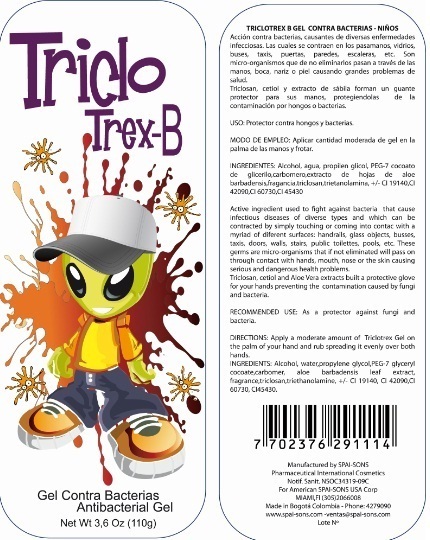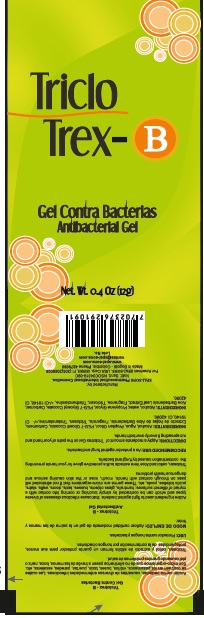 DRUG LABEL: TRICLOTREX-B
NDC: 66854-015 | Form: GEL
Manufacturer: SPAI-SONS PHARMACEUTICAL INTERNATIONAL COSMETICS
Category: otc | Type: HUMAN OTC DRUG LABEL
Date: 20120704

ACTIVE INGREDIENTS: TRICLOSAN 0.3 g/100 g
INACTIVE INGREDIENTS: ALCOHOL; WATER; PROPYLENE GLYCOL; PEG-7 GLYCERYL COCOATE; CARBOMER HOMOPOLYMER TYPE C (ALLYL PENTAERYTHRITOL CROSSLINKED); ALOE VERA LEAF; TROLAMINE; EXT. D&C VIOLET NO. 2; FD&C YELLOW NO. 5; FD&C RED NO. 40; D&C BLUE NO. 4

TRICLOTREX-B ANTIBACTERIAL GEL

ACTIVE INGREDIENT

THIS PRODUCT IS AN ANTIBACTERIAL GEL WHICH PRODUCES A SYNERGISTIC EFFECT BETWEEN THE TRICLOSAN IS THE ACTIVE INGREDIENT WITH A VOLATILE CARRIER SUCH AS ALCOHOL.

PURPOSE

THIS PRODUCT ACT AS A PROTECTOR AGAINST FUNGI AND BACTERIA.

KEEP OUT OF REACH OF CHILDREN

THIS PRODUCT MUST BE KEEP OUT REACH OF EYES CHILDREN.

INDICATIONS AND USAGE

THIS PRODUCT IS FOR TOPICAL APPLICATION,

WARNINGS

IF THIS PRODUCT TO CONTACT WITH EYES RINSE IMMEDIATELY WITH WATER AND CONSULT YOUR DOCTOR

DOSAGE AND ADMINISTRATION

APPLY A MODERATE AMOUNT OF TRICLOTREX GEL ON THE PALM OF YOUR HAND AND RUB SPREADING IT EVENLY OVER BOTH HANDS.

INACTIVE INGREDIENT

TRICLOSAN, CETIOL AND ALOE VERA EXTRACTS BUILT A PROTECTIVE GLOVE FOR YOUR HANDS PREVENTING THE CONTAMINATION CAUSED BY FUNGI AND BACTERIA

IMAGE OF THE LABEL